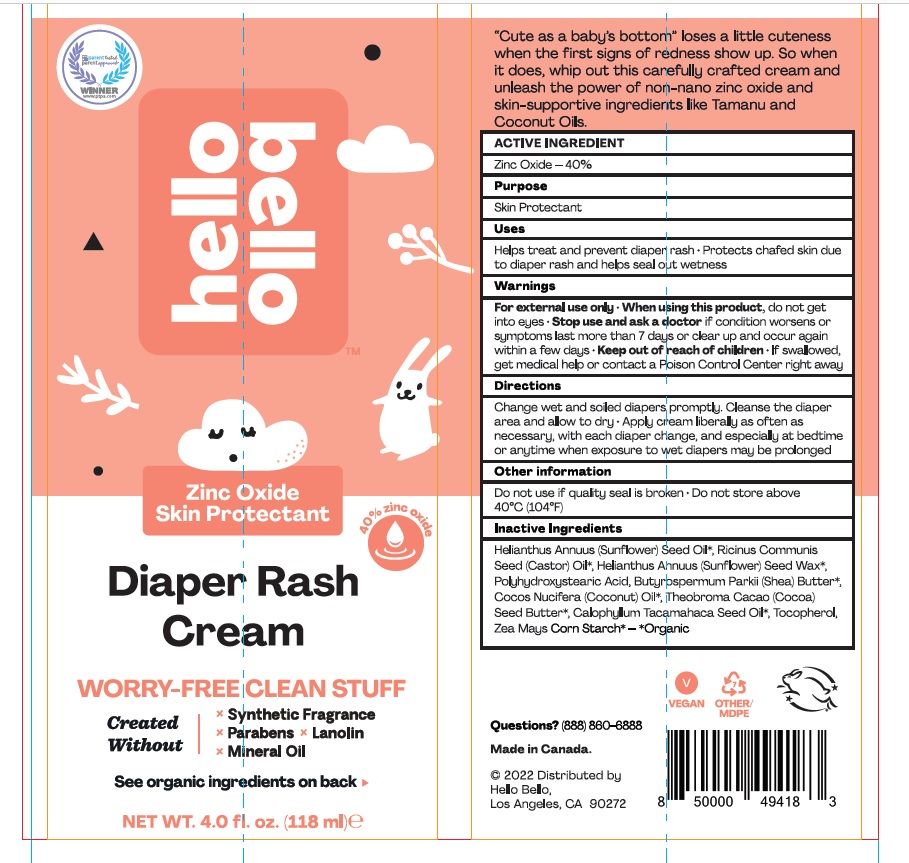 DRUG LABEL: Zinc Oxide 40%
NDC: 50157-477 | Form: CREAM
Manufacturer: BRANDS INTERNATIONAL
Category: otc | Type: HUMAN OTC DRUG LABEL
Date: 20220920

ACTIVE INGREDIENTS: ZINC OXIDE 40 g/100 mL
INACTIVE INGREDIENTS: COCONUT OIL; SHEA BUTTER; COCOA BUTTER; CALOPHYLLUM TACAMAHACA SEED OIL; STARCH, CORN; SUNFLOWER OIL; POLYHYDROXYSTEARIC ACID (2300 MW); CASTOR OIL; HELIANTHUS ANNUUS SEED WAX

Zinc Oxide 40% Diaper Rash Cream

Active Ingredient

Zinc oxide 40%

Purpose

Skin Protectant

Uses

- helps treat and prevent diaper rash
- protects chafed skin due to diaper rash and helps seal out wetness

Warnings

For external use only

When using this product

do not get into eyes

Stop use and ask a doctor if

- condition worsens.
- symptoms last more than 7 days or clear up and occur again within a few days

KEEP OUT OF REACH OF CHILDREN

If swallowed, get medical help or contact a Poison Control Center (1-800-222-1222) right away.

Directions

- change wet and soiled diapers promptly
- cleanse the diaper area
- allow to dry
- apply paste liberally as often as necessary, with each diaper change, especially at bedtime or anytime when exposure to wet diapers may be prolonged

Other Information

- See box for more details

Inactive Ingredients

Sunflower oil, Castor Oil, Sunflower seed wax, polyhydroxystearic acid, shea butter, coconut oil, theobroma cacao seed butter, calophyllum seed oil, tocopherol, zea mays corn starch

Questions and comments?

1-888-880-6888